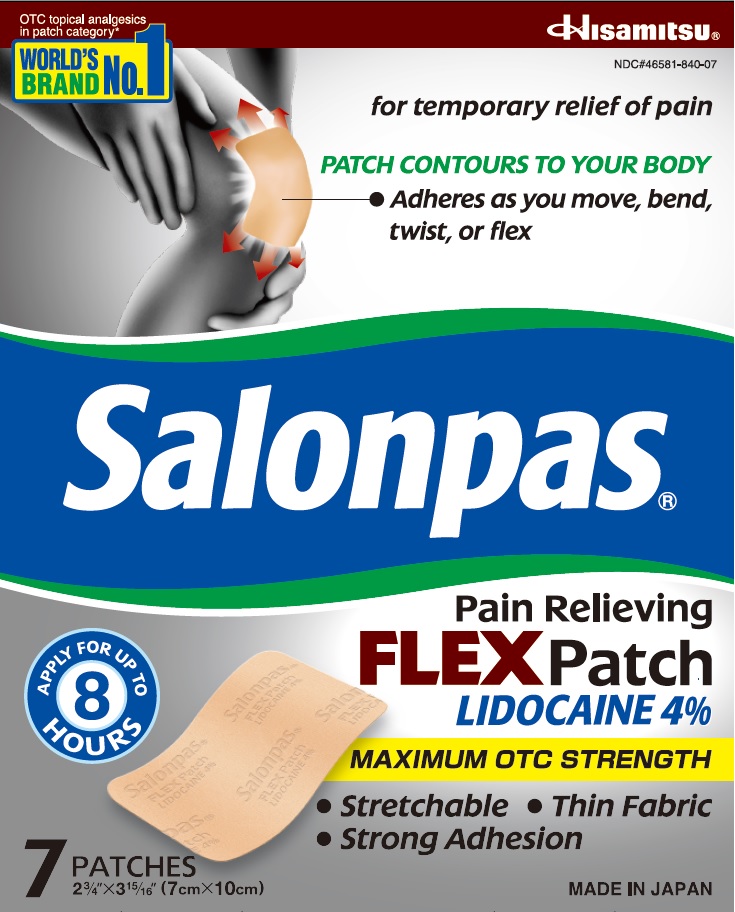 DRUG LABEL: Salonpas Pain Relieving LIDOCAINE 4% FLEX
NDC: 46581-840 | Form: PATCH
Manufacturer: Hisamitsu Pharmaceutical Co., Inc.
Category: otc | Type: HUMAN OTC DRUG LABEL
Date: 20240117

ACTIVE INGREDIENTS: LIDOCAINE 42 mg/1 1
INACTIVE INGREDIENTS: ALUMINUM SILICATE; MINERAL OIL; PROPYLENE GLYCOL

Active ingredient

Lidocaine 4%

Purpose

Topical anesthetic

Uses

For temporary relief of pain

Warnings

For external use only

Do not use

- more than 1 patch at a time
- on wounds or damaged skin
- with a heating pad
- if you are allergic to any igredients of this product

When using this product

- use only as directed
- avoid contact with the eyes, mucous membranes or rashes
- do not bandage tightly

Stop use and ask a doctor if

- skin reactions such as redness, itching, rash, excessive irritation, burning sensation, swelling or blistering occur
- conditions worsen
- symptoms persist for more than 7 days
- symptoms clear up and occur again within a few days

If pregnant or breast-feeding,

ask a health professional before use.

Keep out of reach of children.

If swallowed, get medical help or contact a Poison Control Center right away.

Directions

Adults and children 12 years of age and over:

- clean and dry affected area
- peel film from patch and apply to the skin (see illustration)
- apply 1 patch at a time to affected area, not more than 3 to 4 times daily
- remove patch from the skin after at most 8-hour application

Children under 12 years of age: consult a doctor

Other information

- Avoid storing product in direct sunlight
- Protect product from excessive moisture

Inactive ingredients

aluminum silicate, mineral oil, polyisobutylene, propylene glycol, styrene-isoprene-styrene block copolymer, terpene resin

Questions or comments?

Toll free 1-800-826-8861 www.salonpas.us

Principal Display Panel

OTC topical analgesics in patch category
WORLD’S BRAND NO.1
Hisamitsu
NDC#46581-840-07
for temporary relief of pain
PATCH CONTOURS TO YOUR BODY
Adheres as you move, bend, twist, or flex
Salonpas Pain Relieving FLEX Patch LIDOCAINE 4%
APPLY FOR UP TO 8 HOURS
MAXIMUM OTC STRENGTH
• Stretchable
• Thin Fabric
• Strong Adhesion
7 PATCHES
2 3/4" X 3 15/16" (7cm X 10cm)
MADE IN JAPAN